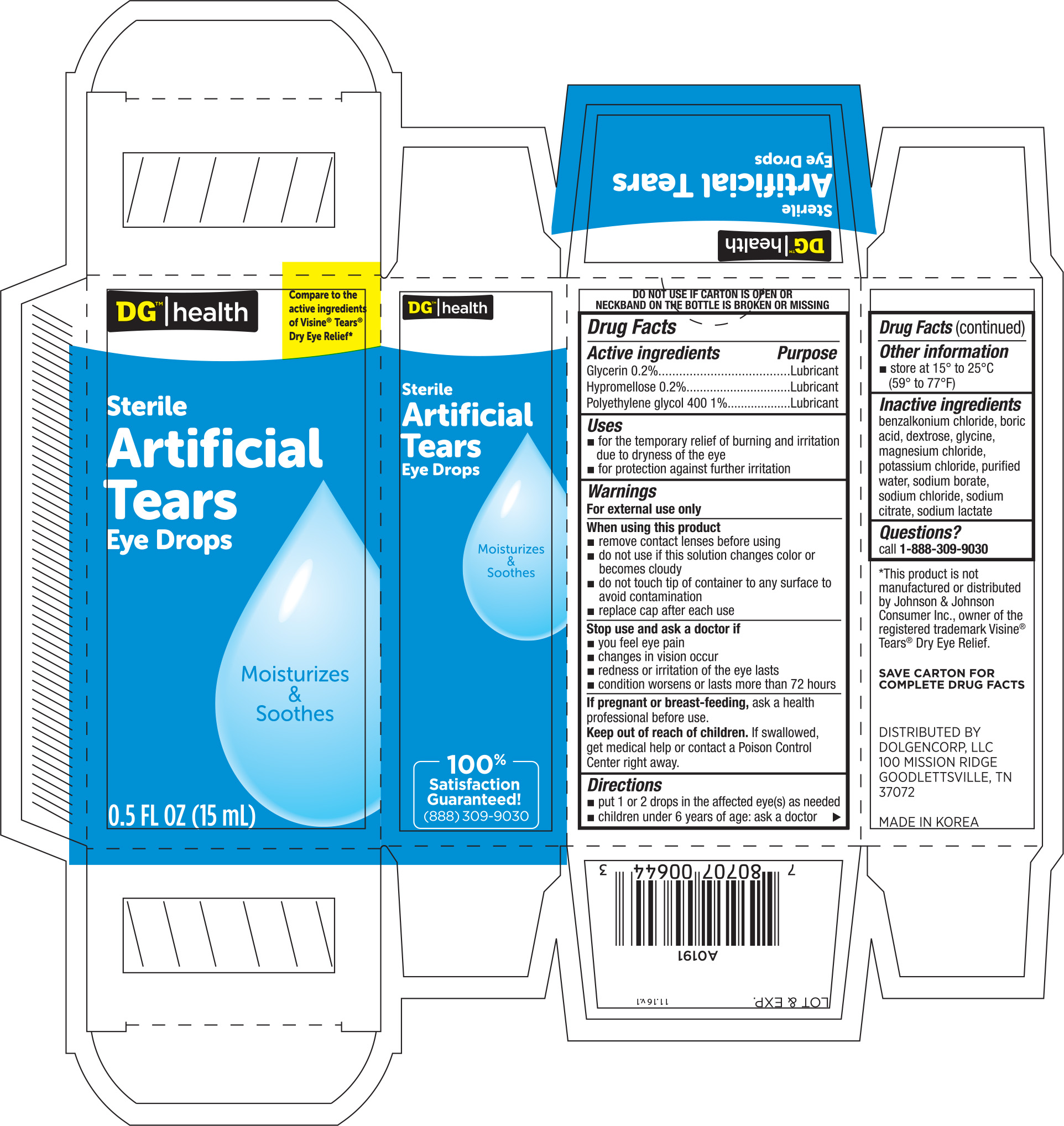 DRUG LABEL: DG Health Artifical Tears
NDC: 55910-644 | Form: SOLUTION/ DROPS
Manufacturer: Dolgencorp Inc.
Category: otc | Type: HUMAN OTC DRUG LABEL
Date: 20171127

ACTIVE INGREDIENTS: GLYCERIN 2.5 mg/1 mL; HYPROMELLOSES 2 mg/1 mL; POLYETHYLENE GLYCOL 400 11.28 mg/1 mL
INACTIVE INGREDIENTS: BENZALKONIUM CHLORIDE; BORIC ACID; DEXTROSE; GLYCINE; MAGNESIUM CHLORIDE; POTASSIUM CHLORIDE; WATER; SODIUM BORATE; SODIUM CHLORIDE; SODIUM CITRATE; SODIUM LACTATE

DG Artificial Tears Eye Drops 0.5oz (NBE Visine Tears) 644

Active ingredients Purpose

Glycerin 0.2%.........................................Lubricant

Hypromellose 0.2%..................................Lubricant

Polyethylene glycol 400 1%.......................Lubricant

Uses

- for the temporary relief of burning and irritation due to dryness of the eye
- for protection against further irritation

Warnings

For external use only

When using this product

- remove contact lenses before using
- do not use if this solution changes color or becomes cloudy
- do not touch tip of container to any surface to avoid contamination
- replace cap after each use

Stop use and ask a doctor if

- you feel eye pain
- changes in vision occur
- redness or irritation of the eyes last
- condition worsens or lasts more than 72 hours

PREGNANCY OR BREAST FEEDING

If pregnant or breast-feeding, ask a health professional before use.

Keep out of reach of children. If swallowed, get medical help or contact a Poison Control Center right away.

Directions

- pute 1 or 2 drops in the affected eye(s) as needed
- children under 6 years of age: ask a doctor

Other information

- store at 15° to 25° (59° to 77°)

Inactive ingredients

benzalkonium chloride, boric acid, dextrose, glycine, magnesium chloride, potassium chloride, purified water, sodium borate, sodium chloride,

sodium citrate, sodium lactate

DOSAGE AND ADMINISTRATION

Distributed by:

Dolgencorp, LLC

100 Mission Ridge

Goodlettsville, TN 37072

Made in Korea